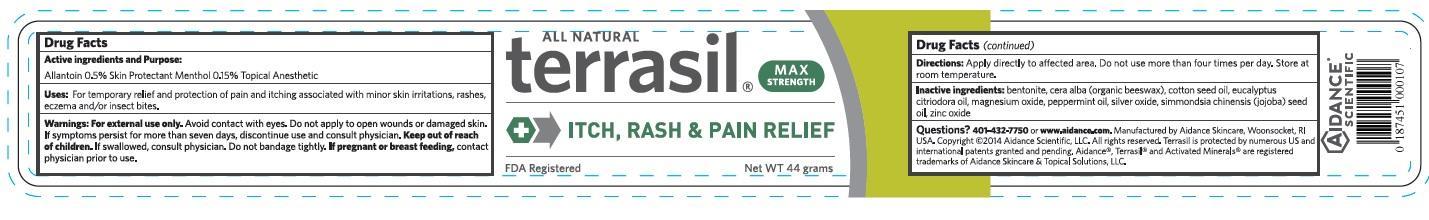 DRUG LABEL: Terrasil Itch, Rash and Pain Relief
NDC: 24909-154 | Form: OINTMENT
Manufacturer: Aidance Skincare & Topical Solutions, LLC
Category: otc | Type: HUMAN OTC DRUG LABEL
Date: 20150716

ACTIVE INGREDIENTS: Allantoin 0.5 g/100 g; MENTHOL 0.15 g/100 g
INACTIVE INGREDIENTS: BENTONITE; COTTONSEED OIL; EUCALYPTUS OIL; JOJOBA OIL; MAGNESIUM OXIDE; PEPPERMINT OIL; SILVER OXIDE; WHITE WAX; ZINC OXIDE

Drug Facts

Active Ingredients

Allantoin 0.5%, Menthol 0.15%

Purpose

Allantoin - Skin Protectant

Menthol - Topical Anesthetic

Uses

For temporary protection and relief of pain and itching associated with minor skin irritations, rashes, eczema and/or insect bites.

Warnings

For external use only. Avoid contact with eyes. Do not apply to open wounds
or damaged skin. If symptoms persist for more than seven days, discontinue use and
consult physician. If swallowed, consult physician. Do not bandage tightly.
If pregnant or breast feeding, contact physician prior to use.

Keep out of reach of children.

If swallowed, consult physician.

Directions

Apply directly to effected area. Do not use more than four
times per day. Store at room temperature.

Inactive Ingredients

bentonite, cera alba (organic beeswax), cotton seed oil, eucalyptus citriodora oil, magnesium oxide, peppermint oil, silver oxide, simmondsia chinensis (jojoba) seed oil, zinc oxide.